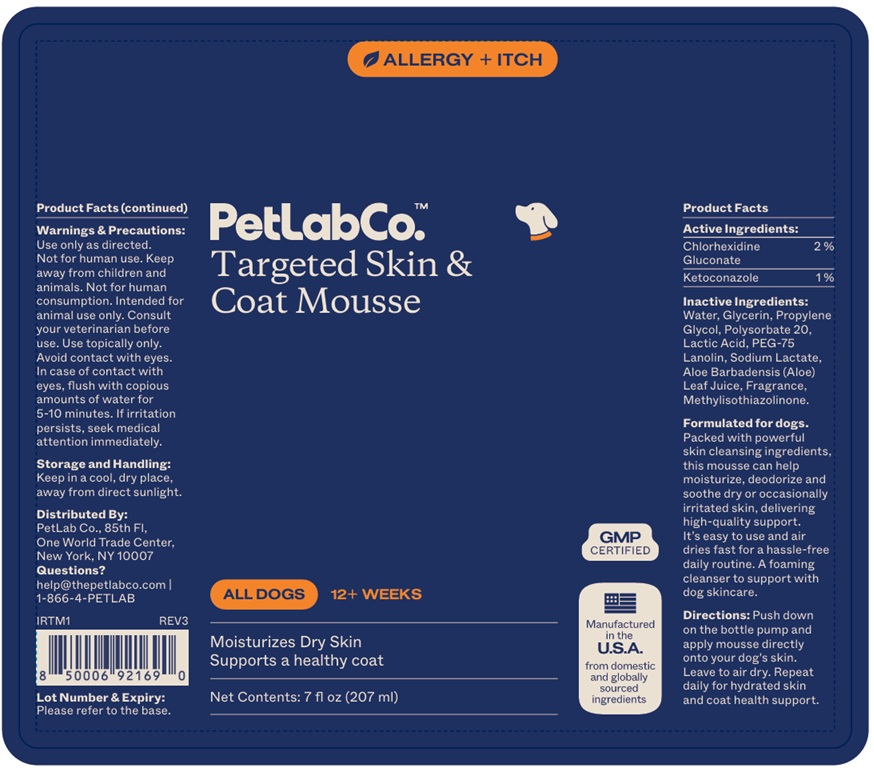 DRUG LABEL: Pet Lab Co. Targeted Skin and Coat Mousse
NDC: 86114-001 | Form: SOLUTION
Manufacturer: Petlab Co.
Category: animal | Type: OTC ANIMAL DRUG LABEL
Date: 20251218

ACTIVE INGREDIENTS: CHLORHEXIDINE GLUCONATE 2 g/100 mL; KETOCONAZOLE 1 g/100 mL
INACTIVE INGREDIENTS: WATER; GLYCERIN; PROPYLENE GLYCOL; POLYSORBATE 20; LACTIC ACID, UNSPECIFIED FORM; PEG-75 LANOLIN; SODIUM LACTATE; ALOE VERA LEAF; METHYLISOTHIAZOLINONE

PetLabCo.™ Targeted Skin & Coat Mousse

Active Ingredients:

Chlorhexidine Gluconate 2%

Ketoconazole 1%

Inactive Ingredients:

Water, Glycerin, Propylene Glycol, Polysorbate 20, Lactic Acid, PEG-75 Lanolin, Sodium Lactate, Aloe Barbadensis (Aloe) Leaf Juice, Fragrance, Methylisothiazolinone.

Directions:

Push down on the bottle pump and apply mousse directly onto your dog's skin. Leave to air dry. Repeat daily for hydrated skin and coat health support.

Warnings & Precautions:

Use only as directed. Not for human use. Keep away from children and animals. Not for human consumption. Intended for animal use only. Consult your veterinarian before use. Use topically only. Avoid contact with eyes. In case of contact with eyes, flush with copious amounts of water for 5-10 minutes. If irritation persists, seek medical attention immediately.

Storage and Handling:

Keep in a cool, dry place, away from direct sunlight.

ALLERGY + ITCH

ALL DOGS

12+ WEEKS

Moisturizes Dry Skin
Supports a healthy coat

GMP CERTIFIED

Manufactured in the U.S.A.
from domestic and globally sourced ingredients

Formulated for dogs.
Packed with powerful skin cleansing ingredients, this mousse can help moisturize, deodorize and soothe dry or occasionally irritated skin, delivering high-quality support. It's easy to use and air dries fast for a hassle-free daily routine. A foaming cleanser to support with dog skincare.

Distributed By:
PetLab Co., 85th Fl,
One World Trade Center,
New York, NY 10007

Questions?
help@thepetlabco.com |
1-866-4-PETLAB

Lot Number & Expiry:

Please refer to the base.